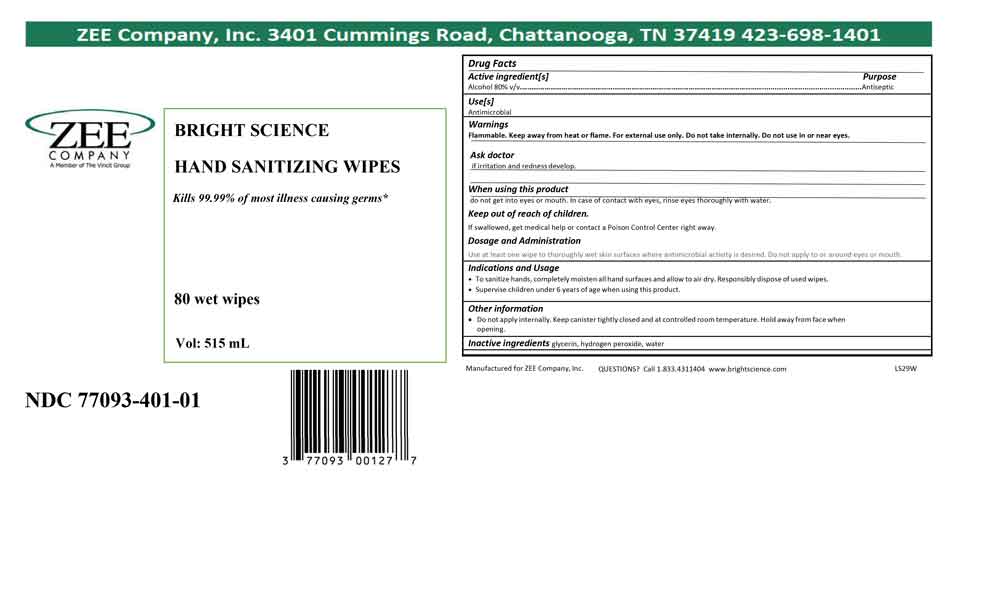 DRUG LABEL: BRIGHT SCIENCE HAND SANITIZING WIPES
NDC: 77093-401 | Form: CLOTH
Manufacturer: Vincit Zee
Category: otc | Type: HUMAN OTC DRUG LABEL
Date: 20210203

ACTIVE INGREDIENTS: ALCOHOL 80 mL/100 mL
INACTIVE INGREDIENTS: GLYCERIN 1.45 mL/100 mL; HYDROGEN PEROXIDE 0.125 mL/100 mL; WATER

LS29W BRIGHT SCIENCE HAND SANITIZING WIPES

ACTIVE INGREDIENT

Alcohol 80% v/v

PURPOSE

Antimicrobial

WARNINGS

Flammable. Keep away from heat or flame. For external use only. Do not take internally. Do not use in or near eyes.

Stop use and ask a doctor if irritation and redness develop.

Stop use and ask a doctor if condition persists or gets worse

When using this product , do not get into eyes or mouth. In case of contact with eyes, rinse eyes thoroughly with water.

Keep out of reach of children. If swallowed, get medical help or contact a Poison Control Center immediately.

INDICATIONS AND USAGE

• To sanitize hands, completely moisten all hand surfaces and allow to air dry. Responsibly dispose of used wipes.
• Supervise children under 6 years of age when using this product.

OTHER SAFETY INFORMATION

• Do not apply internally. Keep canister tightly closed and at controlled room temperature. Hold away from face when opening.

INACTIVE INGREDIENT

water, glycerin, hydrogen peroxide

RECENT MAJOR CHANGES

Indications and Usage changed for accuracy. 02/2021

Dosage and Adminstration changed for accuracy. 02/2021

Indications and Usage heading applied to section previously denoted as Instructions for Use 02/2021

Dosage and Administration section reapplied 02/2021

DOSAGE AND ADMINISTRATION

Use at least one wipe to thoroughly wet skin surfaces where antimicrobial activity is desired. Do not apply to or around eyes or mouth.

PACKAGE LABEL

80 wet wipes NDC: 77093-401-01